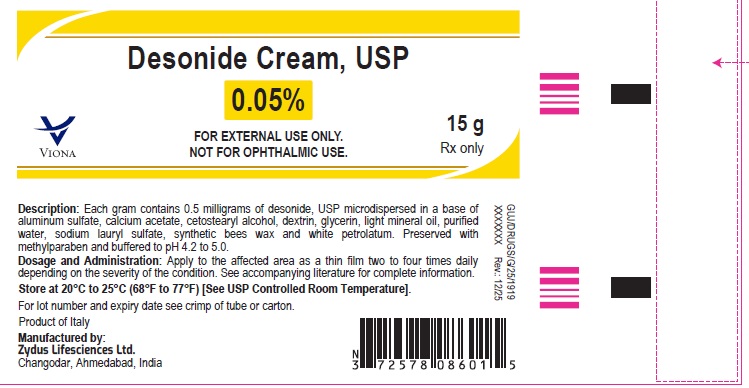 DRUG LABEL: Desonide
NDC: 70771-1381 | Form: CREAM
Manufacturer: Zydus Lifesciences Limited
Category: prescription | Type: HUMAN PRESCRIPTION DRUG LABEL
Date: 20260112

ACTIVE INGREDIENTS: DESONIDE 0.5 mg/1 g
INACTIVE INGREDIENTS: ALUMINUM SULFATE; CALCIUM ACETATE; CETOSTEARYL ALCOHOL; GLYCERIN; ICODEXTRIN; LIGHT MINERAL OIL; METHYLPARABEN; PETROLATUM; SODIUM LAURYL SULFATE; WATER; YELLOW WAX

Desonide Cream USP, 0.05%

PACKAGE LABEL.PRINCIPAL DISPLAY PANEL

NDC 70771-1381-1

Desonide Cream USP, 0.05%

15 g

Rx only